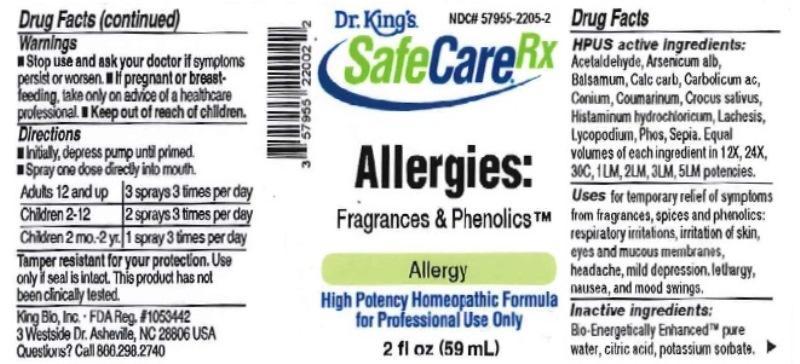 DRUG LABEL: Allergies Fragrances and Phenolics
NDC: 57955-2205 | Form: LIQUID
Manufacturer: King Bio Inc.
Category: homeopathic | Type: HUMAN OTC DRUG LABEL
Date: 20170131

ACTIVE INGREDIENTS: ACETALDEHYDE 12 [hp_X]/59 mL; ARSENIC TRIOXIDE 12 [hp_X]/59 mL; BALSAM PERU 12 [hp_X]/59 mL; OYSTER SHELL CALCIUM CARBONATE, CRUDE 12 [hp_X]/59 mL; PHENOL 12 [hp_X]/59 mL; CONIUM MACULATUM FLOWERING TOP 12 [hp_X]/59 mL; COUMARIN 12 [hp_X]/59 mL; SAFFRON 12 [hp_X]/59 mL; HISTAMINE DIHYDROCHLORIDE 12 [hp_X]/59 mL; LACHESIS MUTA VENOM 12 [hp_X]/59 mL; LYCOPODIUM CLAVATUM SPORE 12 [hp_X]/59 mL; PHOSPHORUS 12 [hp_X]/59 mL; SEPIA OFFICINALIS JUICE 12 [hp_X]/59 mL
INACTIVE INGREDIENTS: WATER; ANHYDROUS CITRIC ACID; POTASSIUM SORBATE

Allergies Fragrances and Phenolics

Drug Facts

____________________________________________________________________________________________________________________

HPUS active ingredients: Acetaldehyde, Arsenicum album, Balsamum peruvianum, Calcarea carbonica, Carbolicum acidum, Conium maculatum, Coumarinum, Crocus sativus, Histaminum hydrochloricum, Lachesis mutus, Lycopodium clavatum, Phosphorus, Sepia. Equal volumes of each ingredient in 12X, 24X, 30C, 1LM, 2LM, 3LM, 5LM potencies.

INDICATIONS AND USAGE

Uses for temporary relief of symptoms from fragrances, spices & phenolics: respiratory irritations, irritation of skin, eyes and mucous membranes, headache, mild depression, lethargy, nausea, and mood swings.

INACTIVE INGREDIENT

Inactive ingredients: Bio-Energetically Enhanced pure water, citric acid, potassium sorbate.

Warnings

- Stop use and ask your doctor if symptoms persist or worsen.
- If pregnant or breast-feeding, take only on advice of a healthcare professional.

- Keep out of reach of children.

Directions:

- Initially, depress pump until primed.
- Spray one dose directly into mouth.
- Adults 12 and up 3 sprays 3 times per day.
- Children 2-12- 2 sprays 3 times per day.
- Children 2 mo.-2yr.- 1 spray 3 times per day.

OTHER SAFETY INFORMATION

Tamper resistant for your protection. Use only if safety seal is intact. This product has not been clinically tested.

PURPOSE

Uses for temporary relief of symptoms from fragrances, spices & phenolics:

- respiratory irritations
- irritation of skin, eyes and mucous membranes
- headache
- mild depression
- lethargy
- nausea
- mood swings